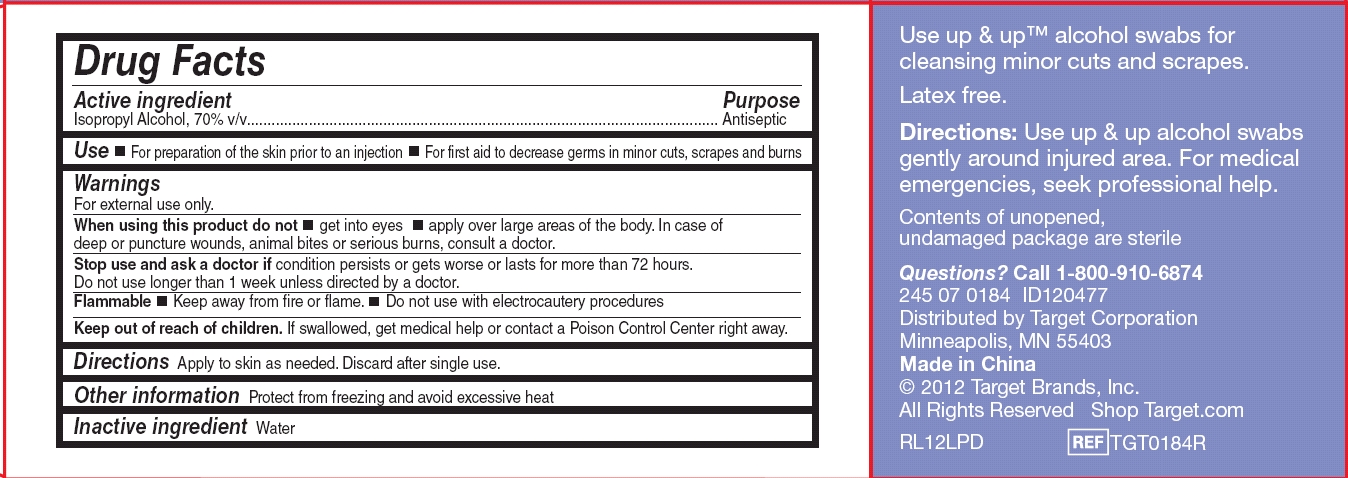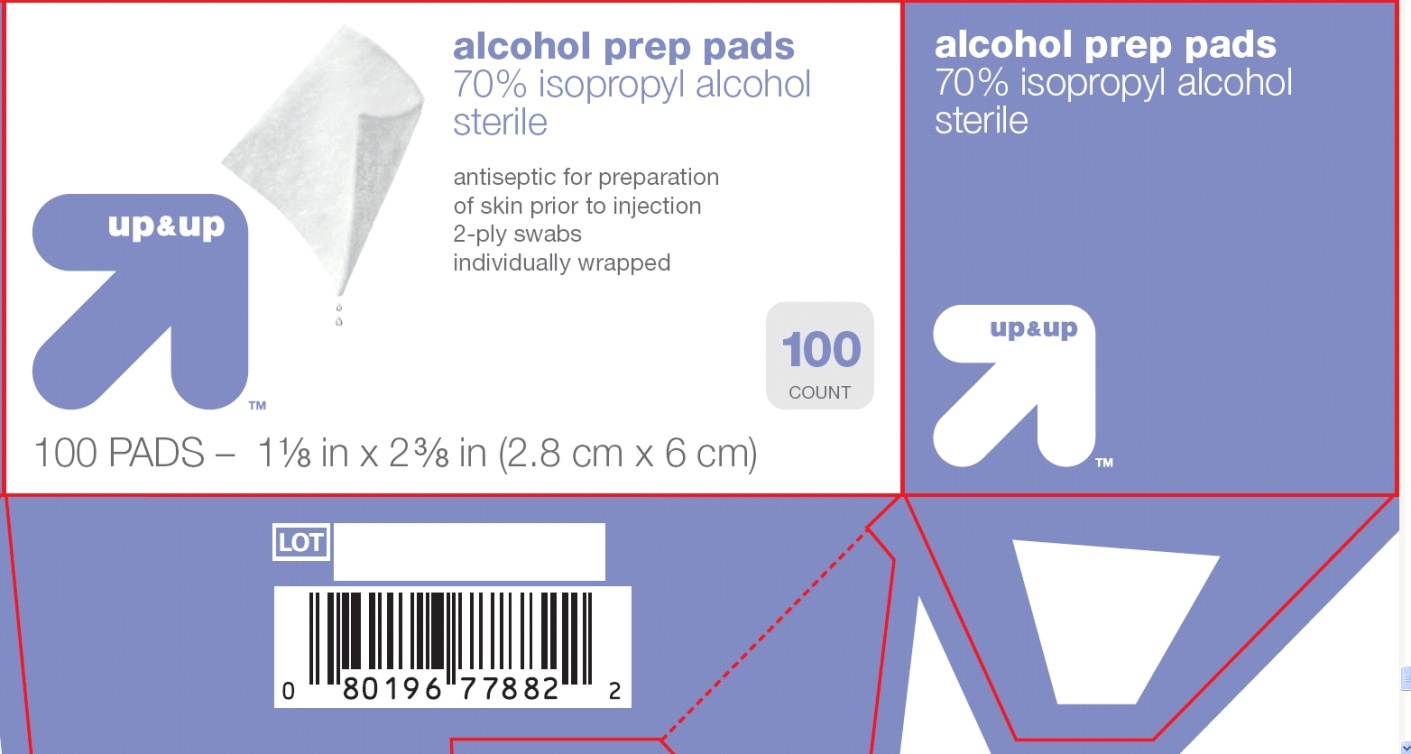 DRUG LABEL: Up and Up alcohol
NDC: 11673-809 | Form: SWAB
Manufacturer: Target Corporation
Category: otc | Type: HUMAN OTC DRUG LABEL
Date: 20131226

ACTIVE INGREDIENTS: ISOPROPYL ALCOHOL 70 mL/100 mL
INACTIVE INGREDIENTS: WATER

Drug Facts

Active ingredient

Isopropyl alcohol, 70% v/v

Purpose

Antiseptic

Uses

- for preparation of the skin prior to injection
- first aid to decrease germs in minor cuts, scrapes and burns

Warnings

For external use only.

When using this product

- do not get into eyes
- do not apply over large areas of the body. In case of deep or puncture wounds, animal bites or serious burns, consult a doctor.

Stop use and ask a doctor if

condition persists or gets worse or lasts for more than 72 hours. Do not use longer than 1 week unless directed by a doctor.

Flammable, keep away from fire or flame.

- Do not use with electrocautery procedures
- Use only in a well ventilated area; fumes may be toxic.

Keep out of reach of children.

If swallowed, get medical help or contact a Poison Control Center right away.

Directions

Apply to skin as needed. Discard after single use.

Other information

Protect from freezing and avoid excessive heat

Inactive ingredients

Water

Package/Label Principal Display Panel

Up&Up

alcohol swabs

70% isopropyl alcohol

sterile

antiseptic for preparation of skin prior to injection

2-ply swabs

individually wrapped

100 COUNT

100 PADS – 1 1/8 in x 2 3/8 in (2.8 cm x 6 cm)

Package/Label Back

Alcohol Swabs back